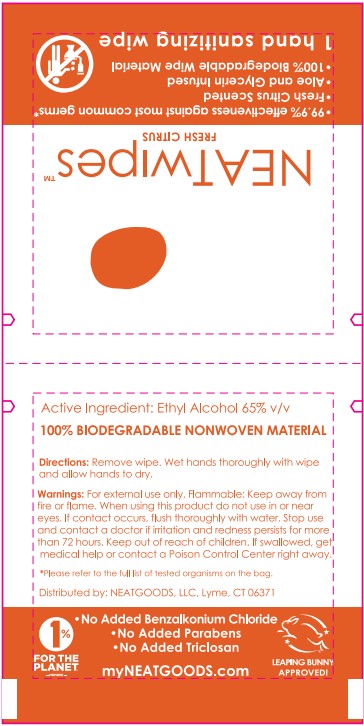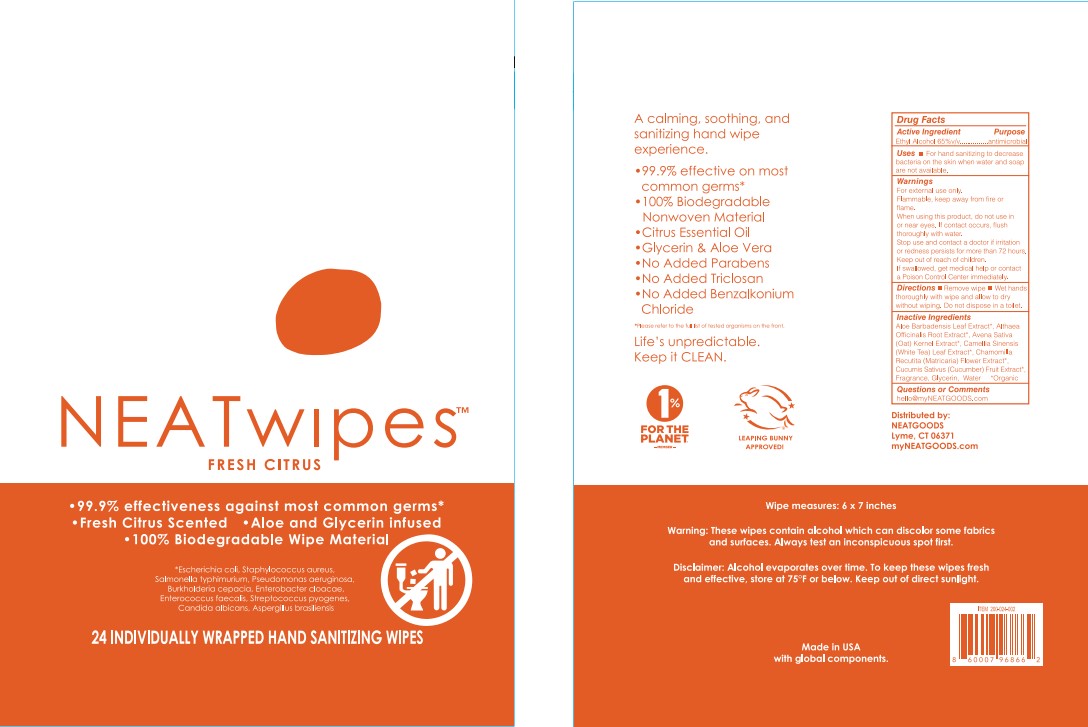 DRUG LABEL: Hand Sanitizer
NDC: 81339-101 | Form: CLOTH
Manufacturer: NeatGoods LLC
Category: otc | Type: HUMAN OTC DRUG LABEL
Date: 20251201

ACTIVE INGREDIENTS: ALCOHOL 65 mL/100 mL
INACTIVE INGREDIENTS: WATER; ALOE VERA LEAF; ALTHAEA OFFICINALIS ROOT; GLYCERIN; CHAMOMILE; CUCUMBER; OAT; GREEN TEA LEAF

NEATGOODS, LLC.
NEATwipes

Active Ingredient

Ethyl Alcohol – 65% v/v

Purpose

Antimicrobial

Uses

• For hand sanitizing to decrease bacteria on the skin when water and soap are not available.

Warnings

For external use only.

Flammable, keep away from fire or flame.

When using this product, do not use in or near eyes.

If contact occurs, flush thoroughly with water.

Stop use and contact a doctor if irritation or redness persists for more than 72 hours.

Keep out of reach of children

If swallowed, get medical help or contact a Poison Control Center immediately.

Directions

• Remove wipe

• Wet hands thoroughly with wipe and allow to dry without wiping.Do not dispose in a toilet,

Inactive Ingredients

Aloe Barbadensis Leaf Extract*, Althaea Officinalis Root Extract*, Avena Sativa (Oat) Kernel Extract*, Camellia Sinensis (White Tea) Leaf Extract*, Chamomilla Recutita (Matricaria) Flower Extract*, Cucumis Sativus (Cucumber) Fruit Extract*, Fragrance, Glycerin, Water *Organic

Questions or Comments

hello@myNEATGOODS.com

Label

NEATwipesTM

FRESH CITRUS

99.9% effectiveness against most common germs*

Fresh Citrus Scented

100% Biodegradable Wipe Material

*Escherichia coli, Staphylococcus aureus,

Salmonella typhimurium, Pseudomonas aeruginosa,

Burkholderia cepacia, Enterobacter cloacae,

Enterococcus Faecalis, Streptococcus pyogenes,

Candida albicans, Aspergillus brasiliensis

24 Individually wrapped hand sanitizing wipes

A calming, soothing, and sanitizing hand wipe experience.

99.9% effective on most common germs*

100% Biodegradable Nonwoven Material

Citrus Essential Oil

Glycerin & Aloe Vera

No Added Parabens

No Added Triclosan

No Added Benzalkonium Chloride

Please refer to the full list of tested organisms on the front

Life's unpredictable.

Keep it CLEAN.

1% FOR THE PLANET-MEMBER-

LEAPING BUNNY APPROVED!

Distributed by:

NEATGOODS Lyme, CT 06371

myNEATGOODS.COM

Wipe measures: 6 x 7 inches

Warning: These wipes contain alcohol which can discolor same fabrics and surfaces. Always test an inconspicuous spot first.

Disclaimer: Alcohol evaporates over time. To keep these wipes fresh and effective, store at 75ºF or below. Keep out of direct sunlight.

Made in USA with global components.

ITEM 200-024-002

8 60007 96866 2

NEATwipesTM

FRESH CITRUS

99.9% effectiveness against most common germs*

Fresh Citrus Scented

Aloe and Glycerin infused

100% Biodegradable Wipe Material

1 hand sanitizing wipe

Active Ingredient: Ethyl Alcohol 65% v/v

100% BIODEGRADABLE NONWOVEN MATERIAL

Directions: Remove wipe. Wet hands thoroughly with wipe and allow hands to dry.

Warnings: For external use only. Flammable: Keep away from fire or flame.

When using this product do not use in or near eyes. If contact occurs, flush thoroughly with water.

Stop use and contact a doctor if irritation and redness persists for more than 72 hours.

Keep out of reach of children. If swallowed, get medical help or contact a Poison Control Center right away.

*Please refer to the full list of tested organisms on the bag.

Distributed by: NEATGOODS Lyme, CT 06371

1% FOR THE PLANET-MEMBER-

No Added Benzalkonium Chloride

No Added Parabens

No Added Triclosan

myNEATGOODS.COM

LEAPING BUNNY APPROVED